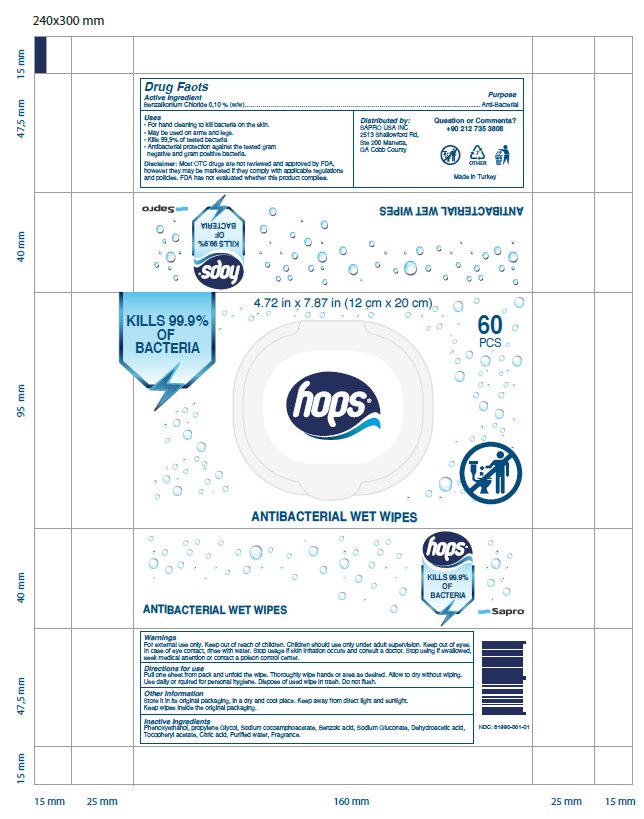 DRUG LABEL: Hops ANTIBACTERIAL WET WIPES
NDC: 81990-001 | Form: CLOTH
Manufacturer: Sapro Temizlik Urunleri Sanayi ve Ticaret Anonim Sirketi
Category: otc | Type: HUMAN OTC DRUG LABEL
Date: 20231230

ACTIVE INGREDIENTS: BENZALKONIUM CHLORIDE 0.1 U/100 U
INACTIVE INGREDIENTS: SODIUM COCOAMPHOACETATE 0.12 U/100 U; DEHYDROACETIC ACID 0.068 U/100 U; .ALPHA.-TOCOPHEROL ACETATE 0.01 U/100 U; PHENOXYETHANOL 0.68 U/100 U; PROPYLENE GLYCOL 0.5 U/100 U; WATER 98.02 U/100 U; BENZOIC ACID 0.102 U/100 U; SODIUM GLUCONATE 0.1 U/100 U; CITRIC ACID MONOHYDRATE 0.05 U/100 U

OTC product listing

Active Ingredient(s)

Alcohol 80% v/v. Purpose: Antiseptic

Purpose

Antiseptic, Hand Sanitizer

Use

Hand Sanitizer to help reduce bacteria that potentially can cause disease. For use when soap and water are not available.

Warnings

For external use only. Flammable. Keep away from heat or flame

Do not use

- in children less than 2 months of age
- on open skin wounds

When using this product keep out of eyes, ears, and mouth. In case of contact with eyes, rinse eyes thoroughly with water.
Stop use and ask a doctor if irritation or rash occurs. These may be signs of a serious condition.
Keep out of reach of children. If swallowed, get medical help or contact a Poison Control Center right away.

Stop use and ask a doctor if irritation or rash occurs. These may be signs of a serious condition.

Keep out of reach of children. If swallowed, get medical help or contact a Poison Control Center right away.

Directions

- Place enough product on hands to cover all surfaces. Rub hands together until dry.
- Supervise children under 6 years of age when using this product to avoid swallowing.

Other information

- Store between 15-30C (59-86F)
- Avoid freezing and excessive heat above 40C (104F)

Inactive ingredients

glycerin, hydrogen peroxide, purified water USP